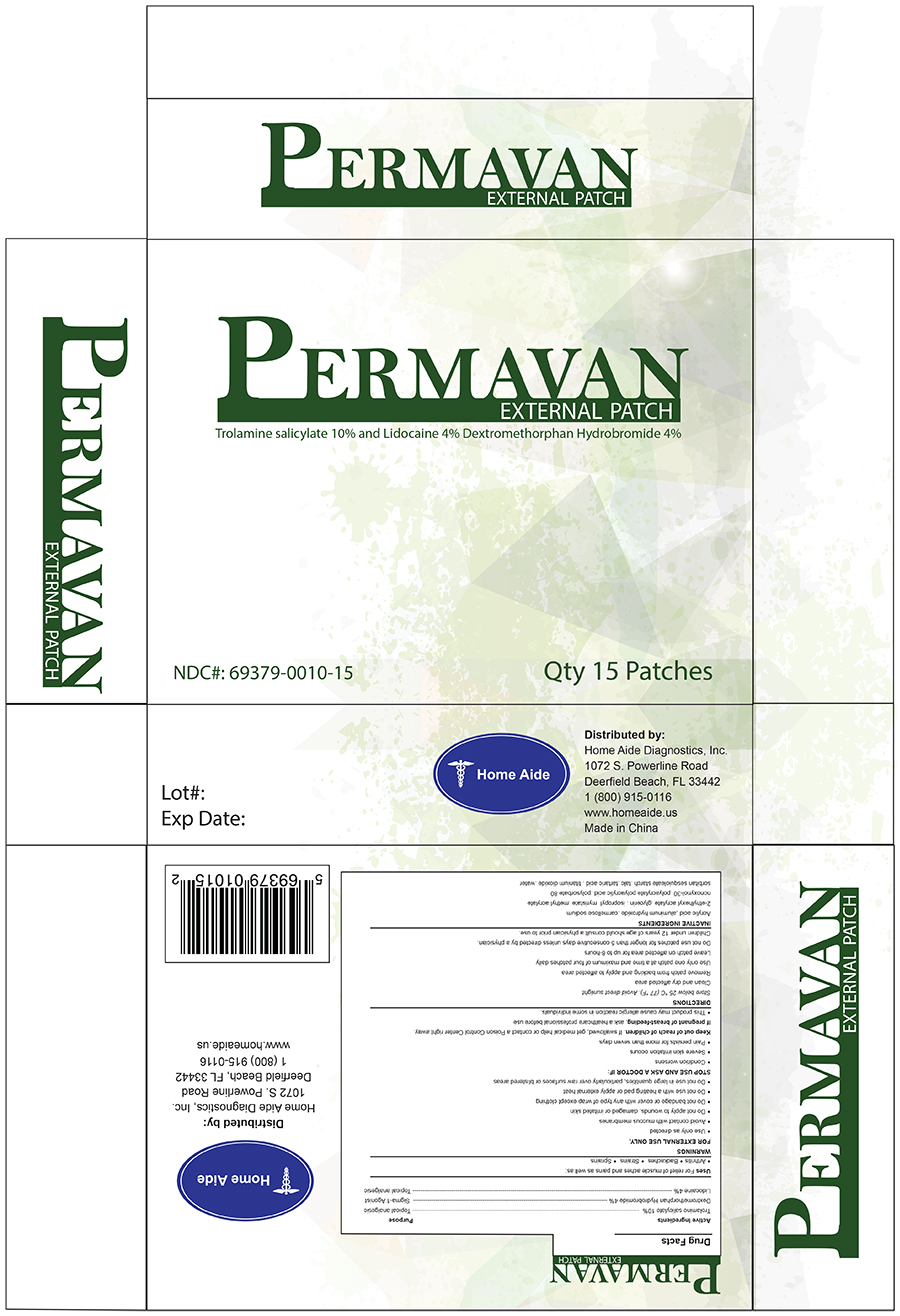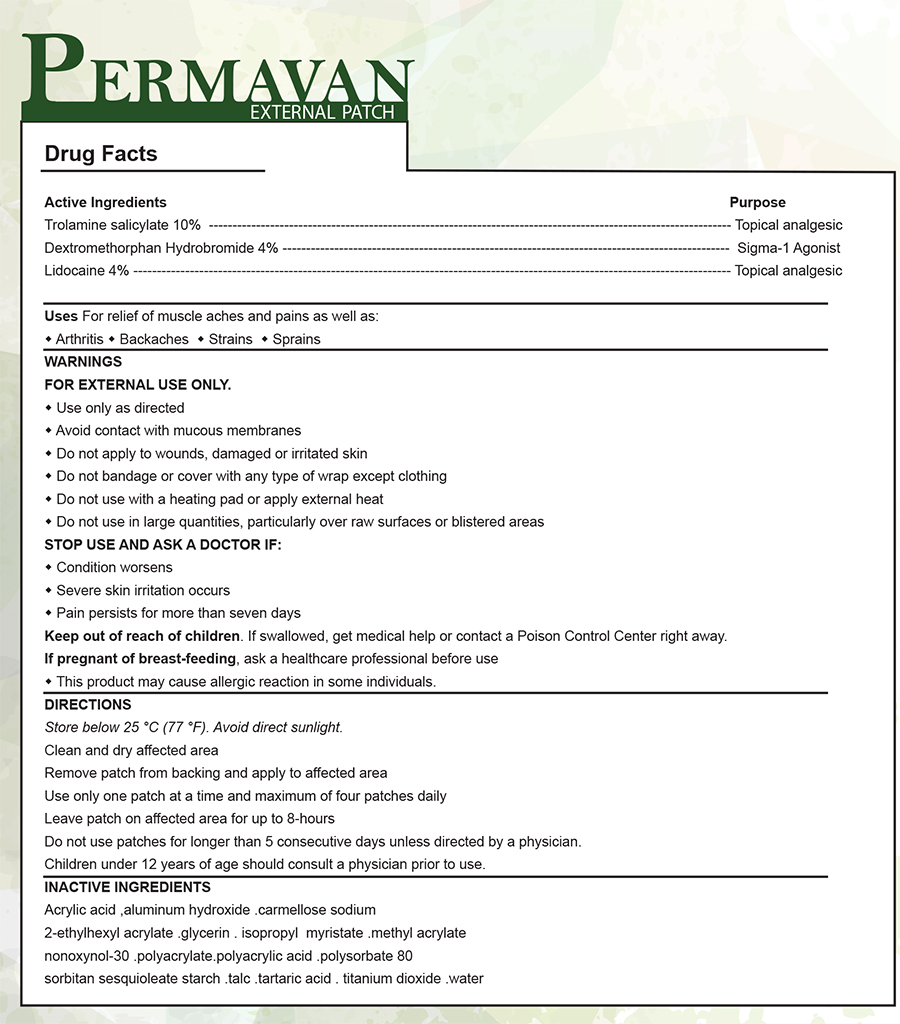 DRUG LABEL: Permavan External Patch
NDC: 69379-010 | Form: PATCH
Manufacturer: Home Aide Diagnostics, Inc.
Category: prescription | Type: HUMAN PRESCRIPTION DRUG LABEL
Date: 20150309

ACTIVE INGREDIENTS: TROLAMINE SALICYLATE 10 g/100 g; LIDOCAINE 4 g/100 g; DEXTROMETHORPHAN HYDROBROMIDE 4 g/100 g

PERMAVAN EXTERNAL PATCH

GENERAL PRECAUTIONS

This product may cause allergic reaction in some individuals.